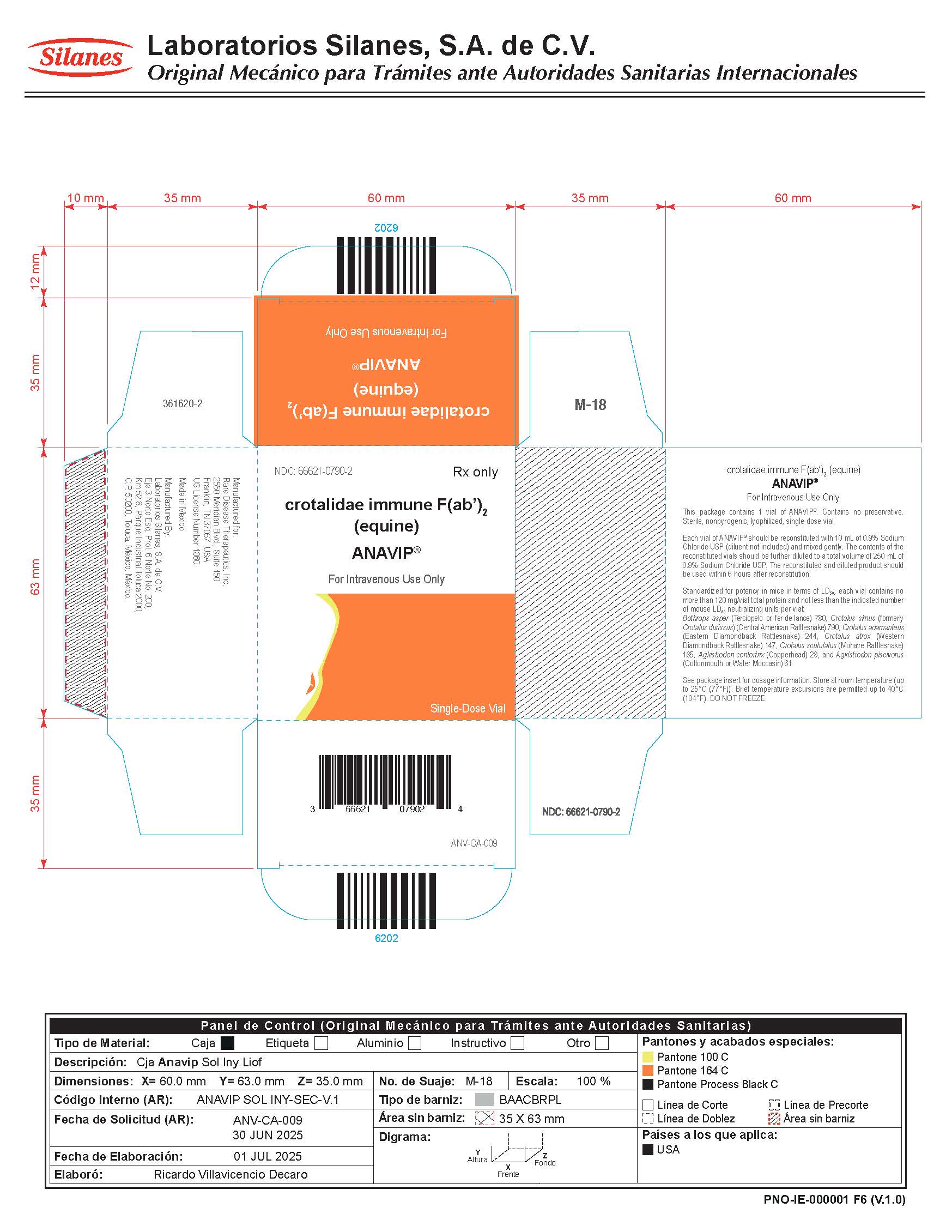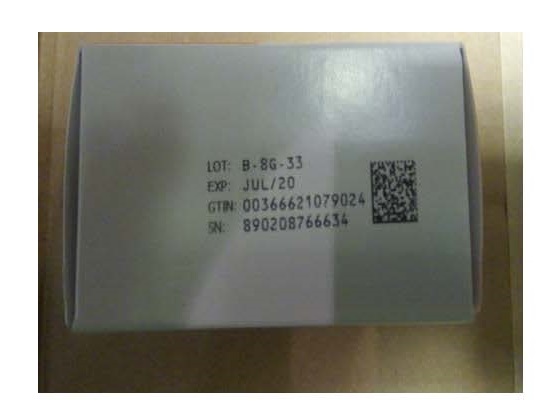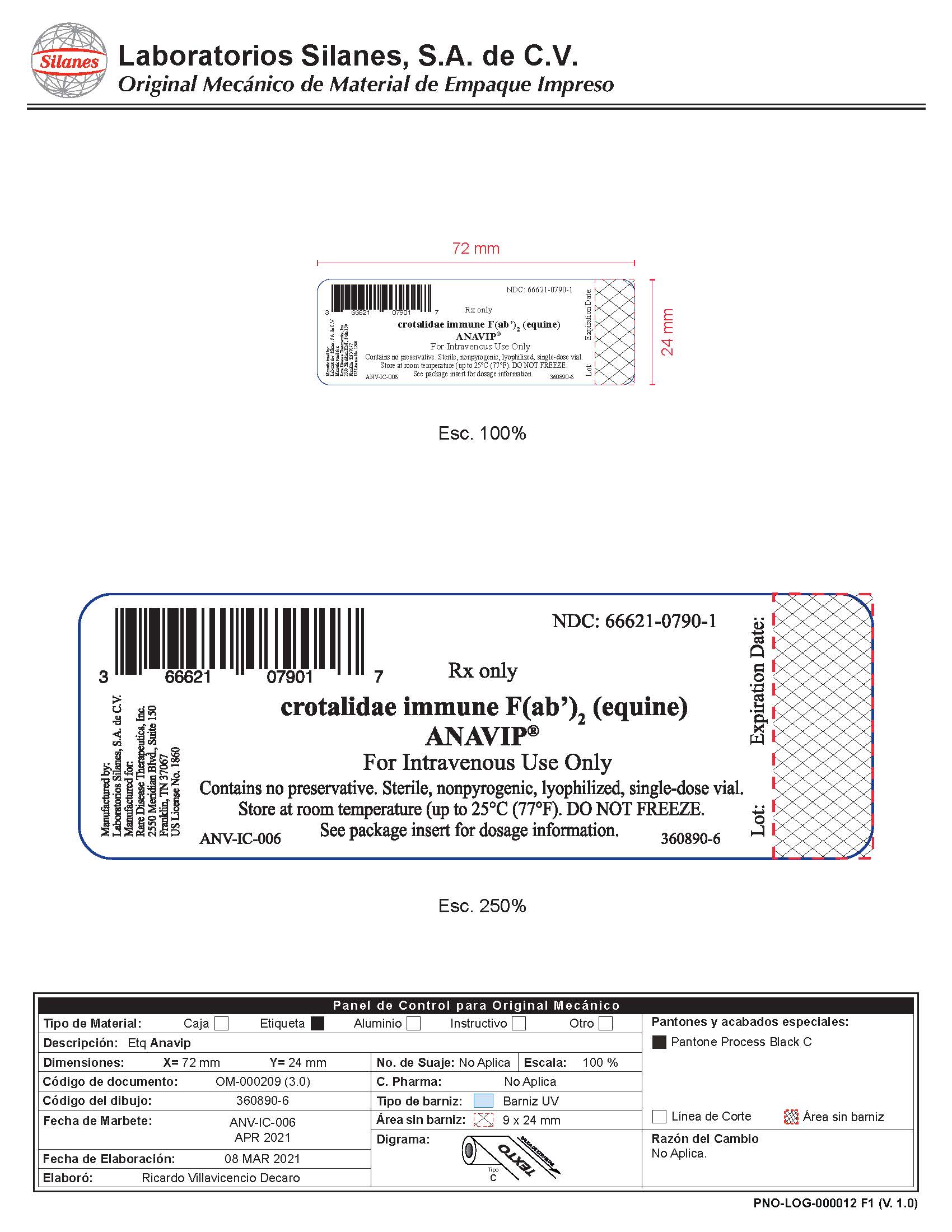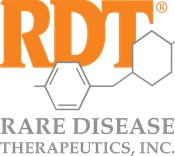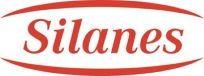 DRUG LABEL: ANAVIP
NDC: 66621-0790 | Form: INJECTION, POWDER, LYOPHILIZED, FOR SOLUTION
Manufacturer: Rare Disease Therapeutics, Inc
Category: other | Type: PLASMA DERIVATIVE
Date: 20260123

ACTIVE INGREDIENTS: PIT VIPER (CROTALINAE) IMMUNE GLOBULIN ANTIVENIN (EQUINE) 12 mg/1 mL

HIGHLIGHTS OF PRESCRIBING INFORMATION

These highlights do not include all the information needed to use ANAVIP safely and effectively. See full prescribing information for ANAVIP.
ANAVIP(R)
crotalidae immune F(ab')2 (equine)
Lyophilized Powder for Solution for Injection
For Intravenous Use Only
Initial U.S. Approval: 2015

RECENT MAJOR CHANGES

Indication and Use (1) April 2021
Dosage and Administration (2) April 2021
Animal Toxicology and/or Pharmacology (13.2) April 2021

1 INDICATIONS AND USAGE

ANAVIP [crotalidae immune F(ab')2 (equine)] is an equine-derived antivenin indicated for the management of adult and pediatric patients with North American Pit Viper envenomation. (1)

2 DOSAGE AND ADMINISTRATION

Intravenous use only.

Dose | No. of Vials | Infusion Rate
Initial Dose | 10 vials | Infuse intravenously over 60 minutes.
Additional dose(s) to achieve initial control | 10 vials (as needed) | Infuse intravenously over 60 minutes.
Observation and late dosing | 4 vials | Infuse intravenously over 60 minutes.

- Initiate administration as soon as possible after North American Pit Viper bite in patients who develop signs of envenomation (e.g., local injury, coagulation abnormality, or systemic signs of envenomation). (2)
- Monitor patients in a health care setting at least 18 hours following initial control of signs and symptoms. Re-emerging symptoms including coagulapathies may be suppressed with an additional 4 vial doses of ANAVIP as needed. (2)
- Reconstitute each vial with 10 milliliters (mL) of sterile normal saline (0.9% NaCl). (2)
- Combine and further dilute to a total of 250 mL with sterile normal saline (0.9% NaCl). (2)

DOSAGE FORMS AND STRENGTHS

Each vial contains a sterile, lyophilized preparation containing not more than 120 milligrams total protein and not less than the indicated number of mouse LD50 neutralizing units (3):

Snake Species Used for Standardization | Minimum Mouse LD50 Units per Vial
Bothrops asper (Terciopelo or fer-de-lance)^1 | 780
Crotalus simus (formerly Crotalus durissus) (Central American Rattlesnake)^1 | 790
Crotalus adamanteus (Eastern Diamondback Rattlesnake) | 244
Crotalus atrox (Western Diamondback Rattlesnake) | 147
Crotalus scutulatus (Mohave Rattlesnake)^2 | 185
Agkistrodon contortrix (Copperhead) | 28
Agkistrodon piscivorus (Cottonmouth or Water Moccasin) | 61

The venom of these species is used in the manufacture of ANAVIP.

The Mohave phenotype A is used for standardization.

CONTRAINDICATIONS

None. (4)

WARNINGS AND PRECAUTIONS

- ANAVIP may cause allergic reactions.

- Patients with known allergies to horse protein are particularly at risk for an anaphylactic reaction. If signs or symptoms of anaphylaxis or hypersensitivity reactions (including urticaria, rash, tightness of the chest, wheezing, hypotension) occur, discontinue immediately and institute appropriate treatment.
- Monitor patients with follow-up visits for signs and symptoms of delayed allergic reactions or serum sickness (rash, fever, myalgia, arthralgia, pruritus, urticarial rash) and treat appropriately if necessary. (5.1)

- ANAVIP is made from equine plasma and may contain infectious agents, e.g., viruses. (5.2)
- Localized reactions and generalized myalgias have been reported with the use of cresol as an injectable excipient. (5.3)

ADVERSE REACTIONS

The most common adverse reactions (>2%) in the clinical trials were: pruritus, nausea, rash, arthralgia, peripheral edema, myalgia, headache, pain in extremity, vomiting and erythema. (6.1)
To report SUSPECTED ADVERSE REACTIONS, contact Rare Disease Therapeutics, Inc., at 1-844-472-7389, or FDA at 1-800-FDA-1088 or www.fda.gov/medwatch.

FULL PRESCRIBING INFORMATION

1 INDICATIONS AND USAGE

ANAVIP [crotalidae immune F(ab')2 (equine)] is an equine-derived antivenin indicated for the management of adult and pediatric patients with North American Pit Viper envenomation.

2 DOSAGE AND ADMINISTRATION

For Intravenous use only.

Administer ANAVIP as soon as possible after North American Pit Viper bite in patients who develop any signs of envenomation (e.g., local injury, coagulation abnormality, or systemic signs of envenomation).
The amount of antivenin required to treat a snake bitten patient is highly variable owing in part to the venom burden, the potency of the venom and the time to health care presentation. Use supportive measures to treat certain manifestations of North American Pit Viper envenomation, such as pain, swelling, hypotension, and wound infection. Contact the local poison control centers for additional individual treatment advice.
Prior to initiating treatment, perform laboratory analyses, including complete blood count, platelet count, PT, PTT, serum fibrinogen level, and routine serum chemistries. Repeat testing at regular intervals to gauge response to therapy and anticipate additional dosing.

Initial Dose: 10 vials

- The initial dose of ANAVIP is 10 vials.
- Reconstitute the contents of each vial with 10 milliliters (mL) of sterile normal saline (0.9% NaCl). Average reconstitution time is 11.8 seconds (range 8-26 seconds) per vial when using continuous gentle swirling.
- Inspect the solution visually for particulate matter and discoloration prior to administration. The solution is expected to be clear to yellow/green and opalescent. Do not use if otherwise discolored or turbid.
- Combine the contents of the reconstituted vials promptly and further dilute to a total volume of 250 mL with sterile normal saline (0.9% NaCl). Fluid volumes may need to be adjusted for very small children or infants. Use reconstituted and diluted product within 6 hours. Discard partially or unused reconstituted and diluted product.
- Infuse intravenously over 60 minutes.

- For the first 10 minutes infuse at a 25-50 mL/hour rate, carefully monitoring for any allergic reactions, including any anaphylactic reactions. Discontinue the infusion if any allergic reaction occurs and institute appropriate emergency treatment. Reassess the risk to benefit before continuing the infusion.
- If no reactions occur, the infusion rate may be incrementally increased to the full 250 mL/hour rate until completion. If there is any allergic reaction at any time, stop the infusion, treat accordingly, and reassess the need to continue ANAVIP.

- Following the completion of infusion, monitor the patient for at least 60 minutes for any allergic reaction and to determine that local signs of envenomation are not progressing (leading edge of local injury not progressing), systemic symptoms are resolved and coagulation parameters have normalized or are trending toward normal.

Additional Dosing to Achieve Initial Control

- Administer additional 10 vial doses if needed to arrest the progressive symptoms and repeat every hour until local signs of envenomation are not progressing, systemic symptoms are resolved and coagulation parameters have normalized or are trending toward normal. There is no known maximum dose.
- Prepare additional loading doses as described above for initial dose.
- Once initial control has been achieved, observe the patient to determine any need for further dosing, as described below.

Observation and late Dosing

- Monitor patients in a health care setting at least 18 hours following initial control of signs and symptoms. Re-emerging symptoms including coagulopathies may be suppressed with additional 4 vial doses of ANAVIP as needed. Reconstitute each vial with 10 mL of sterile normal saline (0.9% NaCl). Combine and further dilute to a total of 250 mL. Infuse intravenously over 60 minutes.

3 DOSAGE FORMS AND STRENGTHS

ANAVIP is supplied as a sterile, lyophilized powder. Each vial contains not more than 120 milligrams (mg) total protein and not less than the indicated number of mouse LD50 neutralizing units:

Table 1. Minimum Potency Units per Vial in Mouse LD50 Units
Snake Species Used for Standardization | Minimum Mouse LD50 Units per Vial
Bothrops asper (Terciopelo or fer-de-lance)^1 | 780
Crotalus simus (formerly Crotalus durissus) (Central American Rattlesnake)^1 | 790
Crotalus adamanteus (Eastern Diamondback Rattlesnake) | 244
Crotalus atrox (Western Diamondback Rattlesnake) | 147
Crotalus scutulatus (Mohave Rattlesnake)^2 | 185
Agkistrodon contortrix (Copperhead) | 28
Agkistrodon piscivorus (Cottonmouth or Water Moccasin) | 61

^1The venom of these species is used in the manufacture of ANAVIP.

^2The Mohave phenotype A is used for standardization.

4 CONTRAINDICATIONS

None.

5.1 Hypersensitivity

ANAVIP may cause allergic reactions.

- Patients with known allergies to horse protein are particularly at risk for an anaphylactic reaction. If signs or symptoms of anaphylaxis or hypersensitivity reactions (including urticaria, rash, tightness of the chest, wheezing, hypotension) occur, discontinue immediately and institute appropriate treatment.
- Monitor patients with follow-up visits for signs and symptoms of delayed allergic reactions or serum sickness (rash, fever, myalgia, arthralgia, pruritus, urticarial rash) and treat appropriately if necessary.^4

5.2 Transmissible Infectious Agents

ANAVIP is made from equine (horse) plasma and may therefore carry a risk of transmitting infectious agents, e.g., viruses.

5.3 Reactions to Cresol

Trace amounts of cresol from the manufacturing process are contained in ANAVIP. Localized reactions and generalized myalgias have been reported with the use of cresol as an injectable excipient.

6 ADVERSE REACTIONS

The most common adverse reactions observed in more than 2 percent (2%) of patients in the clinical trials for ANAVIP were: pruritus, nausea, rash, arthralgia, peripheral edema, erythema, headache, myalgia, pain in extremity, and vomiting.

6.1 Clinical Trials Experience

Because clinical trials are conducted under widely varying conditions, adverse reaction rates observed in the clinical trials of a drug cannot be directly compared to rates in the clinical trials of another drug and may not reflect the rates observed in clinical practice.
A total of 86 patients were treated with ANAVIP, ranging from 2 to 80 years old. The patient population was comprised of 60 males and 26 females. Patients were monitored for signs and symptoms of adverse reactions including acute hypersensitivity reactions and serum sickness. Follow-up interviews were conducted at 5, 8, 15 and 22 days after treatment to assess symptoms of ongoing venom effect, serum sickness, and any other adverse reactions.
Table 2 shows the adverse reactions occurring in patients across all clinical trials for ANAVIP. Seventy-six percent (65/86) of patients receiving ANAVIP reported at least one adverse reaction.

Table 2: Incidence of Adverse Reactions in Clinical Trials of ANAVIP by Body System
Adverse Reaction | ANAVIP [n=86] (%)
Patients Reporting at Least One Adverse Reactions | 65 (76%)
Skin and subcutaneous tissue disorders | 47 (55%)
Pruritus | 37 (43%)
Rash | 10 (12%)
Blister | 4 (5%)
Erythema | 3 (4%)
Gastrointestinal disorders | 28 (33%)
Nausea | 20 (23%)
Vomiting | 5 (6%)
Musculoskeletal and connective tissue disorders | 19 (22%)
Arthralgia | 9 (11%)
Myalgia | 6 (7%)
Pain in extremity | 5 (6%)
General disorders and administration site conditions | 21 (24%)
Edema peripheral | 7 (8%)
Chills | 3 (4%)
Pyrexia | 4 (5%)
Nervous system disorders | 12 (14%)
Headache | 5 (6%)
Psychiatric disorders | 4 (5%)
Anxiety | 2 (2%)
Insomnia | 2 (2%)
Metabolism and nutrition disorders | 4 (5%)
Dehydration | 2 (2%)
Respiratory, thoracic and mediastinal disorders | 5 (6%)
Dyspnea | 1 (1%)
Blood and lymphatic system disorders | 2 (2%)
Thrombocytopenia | 1 (1%)

6.2 Postmarketing Experience

The following adverse reactions have been identified during post approval use of ANAVIP. Because these reactions are reported as monotherapy or in combination with other drugs and voluntarily from a global population of uncertain size, it is not always possible to reliably estimate their frequency or establish a causal relationship to drug exposure.

- Chest Pain/Discomfort
- Flushing
- Hypersensitivity
- Late Thrombocytopenia
- Necrosis
- Prolonged Prothrombin Time
- Tachycardia
- Treatment failure resulting in death
- Urticaria

8.1 Pregnancy

Risk Summary
Animal reproduction studies have not been conducted with ANAVIP. It is also not known whether ANAVIP can cause fetal harm when administered to a pregnant woman or can affect reproduction capacity. In the U.S. general population, the estimated background risk of major birth defects and miscarriage in clinically recognized pregnancies is 2-4% and 15-20% respectively.

8.2 Lactation

Risk Summary
There is no information regarding the presence of ANAVIP in human milk, its effects on the breastfed infant, or its effect on milk production. The developmental and health benefits of breastfeeding should be considered along with the mother’s clinical need for ANAVIP and any potential adverse effects on the breastfed infant from ANAVIP or from the underlying material condition.

8.4 Pediatric Use

Twenty-four percent (21/86) of patients studied in clinical trials were 16 years of age or younger (6 patients were 2 years of age to 5 years of age, 15 patients ranged from at least 5 years of age to 16 years of age). None of the pediatric patients in the phase 3 study experienced a recurrent coagulopathic effect. All adverse reactions in the pediatric patients were non-serious. The most frequent adverse reactions among pediatric patients were nausea and vomiting, itching, and fever. Thus, the safety and efficacy in the pediatric population was not different from adults.

8.5 Geriatric Use

Over nine percent (9%; 8/86) of patients studied in clinical trials were over 65 years of age. The efficacy of ANAVIP in the geriatric population appears comparable to the overall population.

11 DESCRIPTION

ANAVIP [crotalidae immune F(ab')2 (equine)] is a sterile, lyophilized, polyvalent preparation of equine immunoglobulin F(ab')2 fragments, manufactured from the plasma of horses immunized with venom of Bothrops asper and Crotalus simus (formerly Crotalus durissus). The product is obtained by pepsin digestion of horse plasma to remove the Fc portion of immunoglobulin, followed by fractionation and purification steps. The F(ab')2 content is not less than 85%, F(ab') content is not more than 7%, and the product contains less than 5% intact immunoglobulin. Each vial of ANAVIP contains 25.2-56.8 mg of sodium chloride, 47.30 - 91.35 mg of sucrose, and 95.03-183.15 mg of glycine as stabilizers. Trace amounts of pepsin (≤50 ng/vial), cresol (≤0.058 mg/vial), borates (≤1 mg/vial), and sulfates (≤1.7 mg/vial) may be present from the manufacturing process. Each vial contains no more than 120 mg of protein and will be neutralize not less than 780 times the LD50 of Bothrops asper (Terciopelo or fer-de-lance) venom, 790 times the LD50 of Crotalus simus (formerly Crotalus durissus) (Central American Rattlesnake) venom, 244 times the LD50 of Crotalus adamanteus (Eastern Diamondback Rattlesnake) venom, 147 times the LD50 of Crotalus atrox (Western Diamondback Rattlesnake) venom, 185 times the LD50 of Crotalus scutulatus (Mohave Rattlesnake) venom, 28 times the LD50 of Agkistrodon contortrix (Copperhead) venom and 61 times the LD50 of Agkistrodon piscivorus (Cottonmouth or Water Moccasin) venom in a mouse neutralization assay.
The manufacturing procedures that contribute to the reduction of risk of viral transmission include pepsin digestion, ammonium sulfate precipitation/heat treatment and nanofiltration.

12 CLINICAL PHARMACOLOGY

12.1 Mechanism of Action

ANAVIP contains venom-specific F(ab')2 fragments of immunoglobulin G (IgG) that bind and neutralize venom toxins, facilitating redistribution away from target tissues and elimination from the body.^1,2

12.2 Pharmacodynamics

No pharmacodynamic studies were conducted on ANAVIP.

12.3 Pharmacokinetics

Thirteen healthy volunteers each received an intravenous (IV) dose of one vial (one vial = 81.86 mg) of an antivenin comparable to ANAVIP both in composition and manufacturing. On the first day of antivenin administration, blood samples were collected from all subjects at 16 specific time points: 0 (prior to drug infusion), 5, 10, 20, 30, 45, 60, 120, and 480 minutes after drug infusion. Additional samples were drawn just prior to discharge (Day 1), and on days 3, 5, 7, 9, 11, and 21. A two-compartment model best described the concentration-time data. The pharmacokinetic parameters of the antivenin are summarized in Table 3.

Table 3. Pharmacokinetic Parameters of the ANAVIP Antivenin Following a Single IV Dose to Healthy Volunteers (n=13)
Parameters | Units | Mean | SD
Area under plasma concentration vs time curve | AUC0-∞(µg•h/mL) | 4144 | 670
Steady-state volume of distribution | Vss (L) | 3.3 | 0.9
Mean residence time | MRT (h) | 157 | 40
Elimination half-life | Beta-HL (h) | 133 | 53
Total clearance | CL (mL/h) | 22 | 7

13 NONCLINICAL TOXICOLOGY

In a published non-Good Laboratory Practice study^3, ANAVIP and another licensed North American Pit Viper antivenin were tested and cross-reactivity to the venoms of multiple different North American Pit Vipers was demonstrated in rabbits and mice. Animal studies to determine a no observed adverse effect level were unsuccessful due to technical limitations that prevented determination of a systematically toxic dose.

13.2 Animal Toxicology and/or Pharmacology

ANAVIP is standardized by its ability to neutralize the lethal action of each of the 7 venom immunogens following intravenous injection in mice. The potency of the product will vary from batch to batch; however, a minimum number of mouse LD50 neutralizing units against each of the 7 venoms is included in every vial of final product, as shown in Table 1 [see Dosage Forms and Strengths (3)].
ANAVIP was effective in neutralizing the venoms of 7 clinically important North American Pit Vipers in a murine lethality model see Table 1 [see Dosage Forms and Strengths(3)]. The ED50 data demonstrate the number of milligrams of antivenom necessary to neutralize a milligram of venom.

The amount of Anavip necessary to neutralize one milligram of venom was determined in a murine model. The dynamic between the venom and antivenom in a murine model provides a controlled environment to test the cross reactivity of antivenom against a variety of different snake venoms. Unlike the potency assays performed, as shown in Table 1 [see Dosage Forms and Strengths (3)], the effective dose study provides a mg per mg comparison for venoms from 7 species commonly associated with North American Pit Viper envenomations. The results for each species are shown in Table 4.

Table 4. Average ED50 Values for ANAVIP in a Mouse Model When Administered Three LD50 of Venom
Challenge Venom | ED50 (mg antivenin/mg venom)
B. asper (Terciopelo or fer-de-lance) | 1.7
C. simus (formerly C. durissus) (Central American Rattlesnake) | 3.4
C. adamanteus (Eastern Diamondback Rattlesnake) | 2.4
C. atrox (Western Diamondback Rattlesnake) | 2.9
C. scutulatus A^1 (Mohave Rattlesnake) | 14.6
A. contortrix (Copperhead) | 8.0
A. piscivorus (Cottonmouth or Water Moccasin) | 5.0

^1 C. scutulatus A is the Mohave phenotype containing neurotoxic venom

14 CLINICAL STUDIES

Study 1 was a randomized, prospective, open-label, controlled, comparative, multicenter study was conducted in 12 patients aged 18 to 70 years of age with signs of North American Pit Viper envenomation.^6 The subjects received either a licensed North American Pit Viper antivenin as an active control, or ANAVIP. The subjects were dosed until initial control was achieved, followed by maintenance doses. All patients in both treatment groups achieved initial control of local injury and coagulopathy following early antivenin treatment.
In the active control group, at the end of maintenance dosing, 5 of 6 subjects had platelet counts above 150,000/mm^3, and all 6 had fibrinogen levels above 150 mg/dL. During the follow-up phase two patients exhibited platelets below 150,000/mm^3 and fibrinogen below 150 mg/dL, leading to inpatient management with administration of additional doses (one subject received an additional 6 doses (12 vials) and one subject received an additional 4 doses (8 vials)).
In the ANAVIP arm, at the end of maintenance dosing, 5 of 6 subjects had platelet counts above 150,000/mm^3. One subject’s platelets were 114,000/mm^3 and were trending upward, and all 6 had fibrinogen levels above 150 mg/dL. During the follow-up phase, 5 of 6 subjects had platelet counts above 150,000/mm^3, with no downward trend; 1 subject’s platelet count was 127,000/mm^3 on follow-up Day 1, reached 160,000/mm^3 on Day 4, and continued trending upward. All 6 subjects in the ANAVIP group had fibrinogen levels above 150 mg/dL during the follow-up phase. None in the ANAVIP group required rehospitalization or retreatment with ANAVIP.
Study 2 was a randomized, prospective, blinded, controlled, comparative, multicenter study, comparing two ANAVIP regimens with a licensed North American Pit Viper antivenin (comparator) conducted in patients with North American Pit Viper envenomation at 16 sites in the United States. The study had an in-hospital Acute Treatment Phase that included screening and baseline assessments, initial and maintenance dosing, and an outpatient Follow-up Phase that included 4 follow-up visits on Days 5, 8, 15 and 22.
Patients were randomized in a 1:1:1 ratio to one of three groups: ANAVIP with ANAVIP maintenance therapy (Group 1), ANAVIP with placebo maintenance therapy (Group 2), or Comparator product with Comparator product maintenance therapy (Group 3).
Initial dosing consisted of sequential intravenous (IV) doses infused to achieve initial control. If initial control of envenomation was not achieved, treatment was repeated until initial control was attained. Maintenance dosing (4 vials of ANAVIP or placebo [normal saline (0.9% NaCl)], or 2 vials of comparator product) was initiated 6 hours after the start of the last dose required to achieve initial control, and continued every 6 hours for 3 doses.
The Follow-up Phase began immediately after the third maintenance dose. Patients returned to the clinical site on Days 5, 8, and 15 for scheduled follow-up visits. Patients with ongoing signs of envenomation received 4 vials of ANAVIP or 2 vials of Comparator product. Dosing was provided as needed until the patient was stabilized. One hundred twenty-one (121) patients received blinded study drug and were analyzed for safety and efficacy.
The efficacy endpoint was the proportion of patients experiencing a coagulopathic effect as measured on Study Day 5 or 8. Patients were assessed as experiencing a coagulopathic effect if they had any one of the following: absolute platelet levels < 150,000/mm^3 as measured on either Study Day 5 (±1 day) or 8 (±1 day); absolute fibrinogen levels <150 mg/dL as measured on either Study Day 5 (±1 day) or 8 (±1 day); or clinical coagulopathy between end of maintenance dosing and Study Day 5 requiring additional antivenin. The comparison of coagulopathic effect proportions between treatment groups was tested using an exact logistic regression model with terms for treatment and region. Comparisons of the proportion of coagulopathic effect for two levels of ANAVIP versus Comparator product were performed in the following order: ANAVIP with ANAVIP maintenance dose versus Comparator product; then ANAVIP with Placebo maintenance dose versus Comparator product. The number and percentage of patients who experienced a coagulopathic effect is summarized by treatment group in Table 5. The efficacy analysis did not meet the pre-specified statistically defined superiority criterion. However, the percentages of subjects showing prespecified criteria for coagulopathic effect on either Day 5 and/or Day 8 were 10.3% and 5.3% in the Groups 1 and 2 when compared to 29.7% in Group 3 indicating efficacy of ANAVIP in management of coagulopathic effect in patients with North American Pit Viper envenomation.

Table 5. Comparison of Coagulopathic Effect Rates on Study Day 5 or Study Day 8
Experienced Coagulopathic Effect on Either Day 5 or Day 8 | Group 1 ANAVIP/ANAVIP (n=39) | Group 2 ANAVIP/Placebo (n=38) | Group 3 Comparator product (n=37)
Yes | 4 (10.3%) | 2 (5.3%) | 11 (29.7%)
No | 35 (89.7%) | 36 (94.7%) | 26 (70.3%)
Treatment Group (vs. Group 3) Odds Ratio (95% Cl^1) | 0.275 (0.058, 1.048) | 0.135 (0.014, 0.686)

^1Cl= confidence interval
FDA conducted a post hoc analysis to assess the outcomes of the patients who presented with or without baseline coagulopathic effect in the three treatment groups. Using the pre-specified criteria for coagulopathic effect, it was found that ANAVIP/ANAVIP (Group 1) had the highest percentage of baseline coagulopathic subjects among the three groups [41.5% compared with 17.5% and 32.5% for the ANAVIP/Placebo (Group 2) and Comparator product (Group 3), respectively]. Thirty-three percent (33%) of all baseline coagulopathic subjects also experienced coagulopathic effect on either Day 5 or 8, compared to only 6% for baseline non-coagulopathic subjects. Only 18% of the subjects with baseline coagulopathic effect in Group 1 continued to remain coagulopathic at Days 5 or 8 compared to 58% in Group 3 (Table 6).

Table 6. Coagulopathy by Treatment Group and Baseline Coagulopathy
Baseline Coagulopathy and Experienced coagulopathy on either Day 5 or 8 | Group 1 ANAVIP/ANAVIP | Group 2 ANAVIP/Placebo | Group 3 Comparator product | Total
Number of subjects | n=17 | n=7 | n=12 | n=36
Yes | 3 (17.65%) | 2 (28.57%) | 7 (58.33%) | 12 (33.3%)
No | 14 (82.35%) | 5 (71.43%) | 5 (41.67%) | 24 (66.7%)
No Baseline Coagulopathy and Experienced coagulopathy on either Day 5 or 8 | Group 1 ANAVIP/ANAVIP | Group 2 ANAVIP/Placebo | Group 3 Comparator product | Total
Number of Subjects | n=22 | n=31 | n=25 | n=78
Yes | 1 (4.55%) | 0 (0%) | 4 (16%) | 5 (6.4%)
No | 21 (95.45%) | 31 (100%) | 21 (84%) | 73 (93.6%)

An exact logistic regression analysis adjusting for baseline coagulopathic effect and region was conducted and showed that treatment effect for both Groups 1 and 2 is statistically significant (Table 7). This analysis provides supportive evidence of the efficacy of ANAVIP.

Table 7. Comparison Coagulopathic Effect Rates Adjusted for Baseline Coagulopathy
 | Group 1 ANAVIP/ANAVIP (n=39) | Group 2 ANAVIP/Placebo (n=38)
Treatment Group (vs Comparator product) Odds ration (95% Cl^1) | 0.184 (0.033, 0.794) | 0.121 (0.010, 0.764)

^1Cl= confidence interval
Analysis by snakebite type was performed but was limited due to the number of unknown snakebite types (n=43). However, 57 subjects who were envenomated by rattlesnakes showed more severe coagulopathic effects and resolution of these effects after treatment with ANAVIP as compared to 21 subjects who were envenomated by copperhead snakes. Due to limited coagulopathic effects in the copperhead snake bite subgroup, efficacy outcomes for late coagulopathies could not be evaluated.

15 REFERENCES

1. Seifert SA and Boyer LV: Recurrence phenomena after immunoglobulin therapy for snake envenomation: Part 1. Pharmacokinetics and pharmacodynamics of immunoglobulin antivenoms and related antibodies. Annals of Emergency Medicine 37(2):189-195; 2001.

2. Boyer LV, Seifert SA and Cain JS: Recurrence phenomena after immunoglobulin therapy for snake envenomation: Part 2. Guidelines for clinical management with crotaline Fab antivenom. Annals of Emergency Medicine 37(2):196-201; 2001.

3. Sanchez EE, Galan JA, Perez JC, et al. The efficacy of two antivenoms against the venom of North American snakes, Toxicon 41: 357-365; 2003.

4. Gold BS, Dart RC and Barish RA: Bites of venomous snakes. New England Journal of Medicine 347(5):347-56; 2002.

5. Boyer LV, Seifert SA, Clark RF, et al: Recurrent and persistent coagulopathy following Pit Viper envenomation. Archives of Internal Medicine 159:706-710; 1999.

6. Boyer LV, Chase PB, Degan JA, et al: Subacute coagulopathy in a randomized, comparative trial of Fab and F(ab’)2 antivenoms. Toxicon 74: 101-108; 2013.

16 HOW SUPPLIED/STORAGE AND HANDLING

ANAVIP is supplied as a sterile, lyophilized preparation in a single-dose vial. When reconstituted with 10 mL of 0.9% NaCl solution, each vial contains not more than 12 mg per mL of protein, and will neutralize not less than 780 times the LD50 of Bothrops asper (Terciopelo or fer-de-lance) venom and 790 times the LD50 of Crotalus simus (formerly Crotalus durissus) (Central American Rattlesnake) venom, 244 times the LD50 of Crotalus adamanteus (Eastern Diamondback Rattlesnake) venom, 147 times the LD50 of Crotalus atrox (Western Diamondback Rattlesnake) venom, 185 times the LD50 of Crotalus scutulatus (Mohave Rattlesnake) venom, 28 times the LD50 of Agkistrodon contortrix (Copperhead) venom and 61 times the LD50 of Agkistrodon piscivorus (Cottonmouth or Water Moccasin) venom in a mouse neutralization assay.

Each carton NDC 66621-0790-2 contains 1 vial of ANAVIP NDC 66621-0790-1.

- Store at room temperature (up to 25 ºC (77 ºF)). Brief temperature excursions are permitted up to 40 ºC (104ºF).
- DO NOT FREEZE.
- Use within 6 hours after reconstitution.
- Discard partially used vials.

17 PATIENT COUNSELING INFORMATION

- Advise patients to contact their physician immediately if they experience unusual bruising or bleeding (e.g., nosebleeds, excessive bleeding after brushing teeth, the appearance of blood in stools or urine, excessive menstrual bleeding, petechiae, excessive bruising or persistent oozing from superficial injuries) after hospital discharge.^5
- Serious Allergic Reactions
  o Advise patients to contact their physician immediately if they experience any signs and symptoms of delayed allergic reactions or serum sickness (e.g., rash, fever, myalgias, arthralgia, pruritus, urticaria) after hospital discharge [see Hypersensitivity (5.1)].^4

Manufactured by:
Laboratorios Silanes S.A. de C.V.
Toluca, Estado de Mexico, Mexico
Silanes® and the Silanes logo are registered trademarks in Mexico of Laboratorios Silanes, S.A. de C.V.

Manufactured for:
Rare Disease Therapeutics, Inc.
2550 Meridian Blvd., Suite 150
Franklin, TN 37067
www.raretx.com
RDT® and the RDT logo are registered trademarks of Rare Disease Therapeutics, Inc.

U.S. License No. 1860

RDT Part No. ANV-PI-009

Silanes Part number: 360893-8

PACKAGE LABEL

Anavip Carton label

Serialization Example of Anavip Carton label

Anavip Vial label